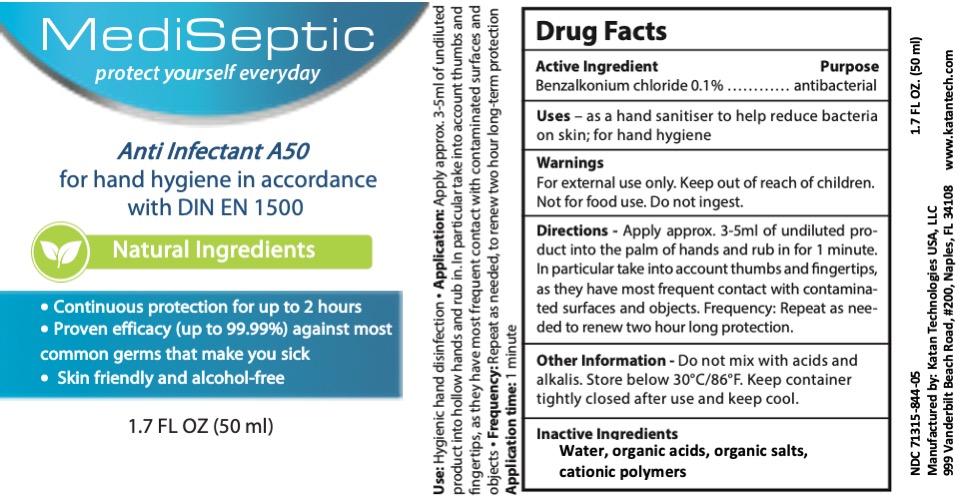 DRUG LABEL: MediSeptic Antinfectant
NDC: 71315-800 | Form: LIQUID
Manufacturer: Katan Technologies USA, LLC
Category: otc | Type: HUMAN OTC DRUG LABEL
Date: 20200526

ACTIVE INGREDIENTS: BENZALKONIUM CHLORIDE 0.1 g/100 g
INACTIVE INGREDIENTS: SALICYLIC ACID 0.25 g/100 g; POVIDONE K15 0.24 g/100 g; CALCIUM FLUORIDE 0.01 g/100 g; GLYCERIN 0.9 g/100 g; WATER 98.5 g/100 g

MediSeptic Anti Infectant Hand Sanitizer

Mediseptic

Application:

Apply approx. 3-5ml of undiluted product into hollow hands and rub in. In particular take into account thumbs and fingertips, as they have most frequent contact with contaminated surfaces and objects.

Frequency: Repeat as needed, to renew two hour long term protection.

Application time: 1 minute

Mediseptic

Inactive Ingredients:

Water

Organic acids

ORganic polymers

Glycerin

MediSeptic

Use:

Hygienic hand disinfection

Use disinfectant safely. Always read label and product information before use.

Mediseptic

Active Ingredient:

Benzalkonium chloride ....0.1% ............antibacterial

Mediseptic

Safety information:

• Keep out of reach of children.

Purpose:

antimicrobial

for hand sanitizing

Mediseptic

Warnings

For external use only.

Keep out of reach of children.

Not for food use.

Do not ingest.

Mediseptic

• Keep out of reach of children.

• Do not mix with acids and alkalis.

• Store below 30C/86F.

• Dispose of empty container in accordance with local regulations.

• Safety data sheet available upon request.

• Keep container tightly closed after use and keep cool.

MediSeptic Anitinfectant

MediSeptic

protect yourself everyday

Anti Infectant Spray

for hygienic hand disinfection in accordance with DIN EN 1500

120 Min. Long-Term Efficacy

• Continuous protection for 2 hours

• Proven efficacy against bacteria and viruses (99.999%)

• Skin-friendly and alcohol-free

Use:

Hygienic hand disinfection

Application:

Apply approx. 3-5ml of undiluted product into hollow hands and rub in. In particular take into account thumbs and fingertips, as they have the most frequent contact with contaminated surfaces and objects.

Frequency: Repeat as needed, to renew two-hour long term protection.

Application time: 1 minute

Safety information:

• Keep out of reach of children.

• Do not mix with acids and alkalis.

• Store below 30C/86F.

• Dispose of empty container in accordance with local regulations.

• Safety data sheet available upon request.

• Keep container tightly closed after use and keep cool.

Non-hazardous substance according to CLP-regulation

Alcohol-free

Non-toxic

Without surfactants and aldehydes

Non-flammable

Use disinfectant safely. Always read label and product information before use.